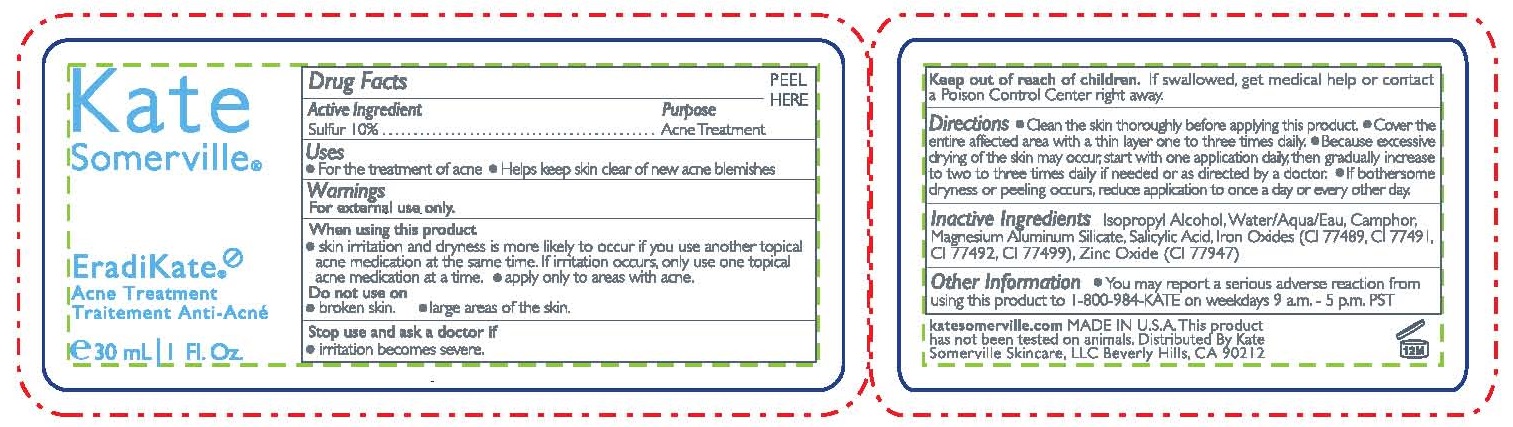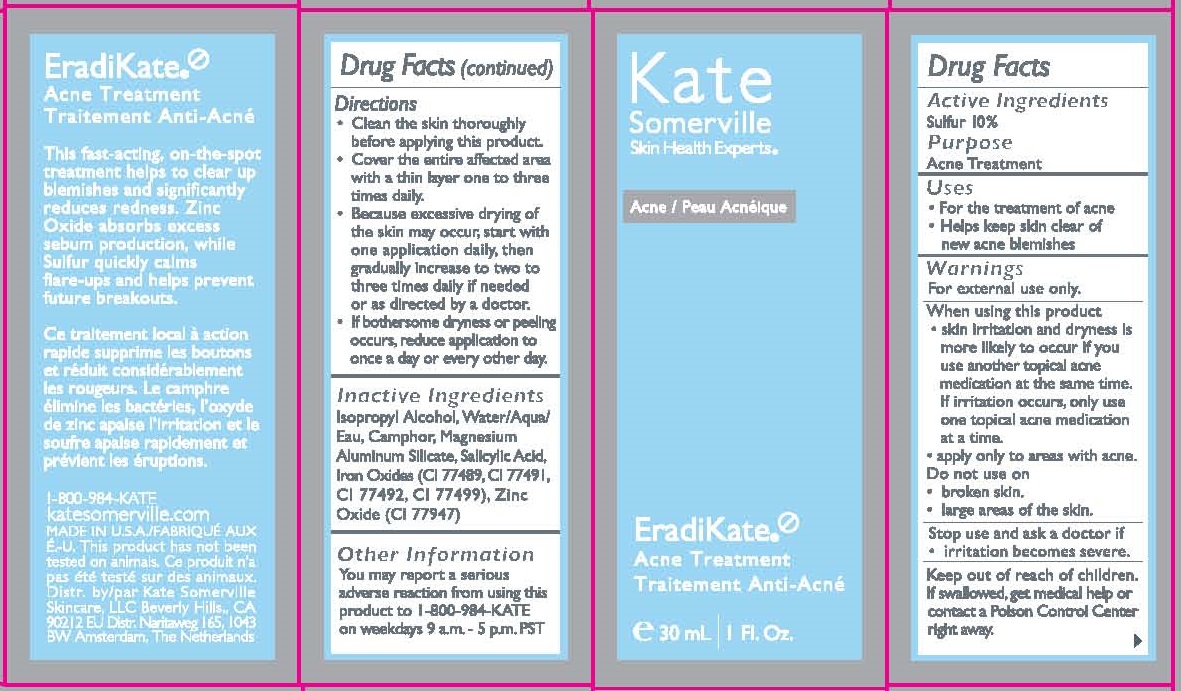 DRUG LABEL: EradiKate ACNE TREATMENT
NDC: 72204-901 | Form: LIQUID
Manufacturer: Rare Beauty Brands Inc
Category: otc | Type: HUMAN OTC DRUG LABEL
Date: 20251201

ACTIVE INGREDIENTS: SULFUR 10 g/100 mL
INACTIVE INGREDIENTS: ISOPROPYL ALCOHOL; WATER; CAMPHOR (NATURAL); MAGNESIUM ALUMINUM SILICATE; SALICYLIC ACID; FERROUS OXIDE; FERRIC OXIDE RED; FERRIC OXIDE YELLOW; FERROSOFERRIC OXIDE; ZINC OXIDE

Kate Somerville (as PLD) - EradiKate Acne Treatment (43479-106)

ACTIVE INGREDIENTS:

SULFUR, 10%

PURPOSE

ACNE TREATMENT

USES

- FOR THE TRETAMENT OF ACNE
- HELPS KEEP SKIN CLEAR OF NEW ACNE BLEMISHES

WARNINGS

FOR EXTERNAL USE ONLY

WHEN USING THIS PRODUCT

- USING OTHER TOPICAL ACNE MEDICATION AT THE SAME TIME OR IMMEDIATELY FOLLOWING THE USE OF THIS PRODUCT MAY INCREASE DRYNESS OR IRRITATION OF THE SKIN. IF THIS OCCURS, ONLY ONE MEDICATION SHOULD BE USED UNLESS DIRECTED BY A DOCTOR.
- AVOID CONTACT WITH EYES. IF EXCESSIVE SKIN IRRITATION DEVELOPS OR INCREASES, DISCONTINUE USE AND CONSULT A DOCTOR.

STOP USE AND ASK A DOCTOR IF SKIN IRRITATION OCCURS.

KEEP OUT OF REACH OF CHILDREN. IF SWALLOWED, GET MEDICAL HELP OR CONTACT A POISON CONTROL CENTER RIGHT AWAY.

DIRECTIONS

- CLEANSE SKIN THOROUGHLY BEFORE APPLYING. COVER THE AFFECTED AREA WITH A THIN LAYER 1 TO 3 TIMES A DAY. BECAUSE EXCESSIVE DRYING OF THE SKIN MAY OCCUR, START WITH 1 APPLICATION DAILY, THEN GRADUALLY INCREASE TO 2 OR 3 TIMES DAILY IF NEEDED OR AS DIRECTED BY A DOCTOR. IF BOTHERSOME DRYNESS OR PEELING OCCURS, REDUCE APPLICATION TO ONCE A DAY OR EVERY OTHER DAY.

OTHER INFORMATION

- DO NOT USE THIS PRODUCT IF YOU HAVE VERY SENSITIVE SKIN OR IF YOU ARE SENSITIVE TO SULFUR.
- YOU MAY REPORT A SERIOUS ADVERSE REACTION FROM USING THIS PRODUCT TO 1-800-981-KATE ON WEEKDAYS 9A.M.-5P.M. PACIFIC TIME.

INACTIVE INGREDIENT

ISOPROPYL ALCOHOL, WATER/AQUA/EAU, CAMPHOR, MAGNESIUM ALUMINUM SILICATE, SALICYLIC ACID, IRON OXIDES (CI 77489, CI 77491, CI 77492, CI 77499), ZINC OXIDE (CI 77947)